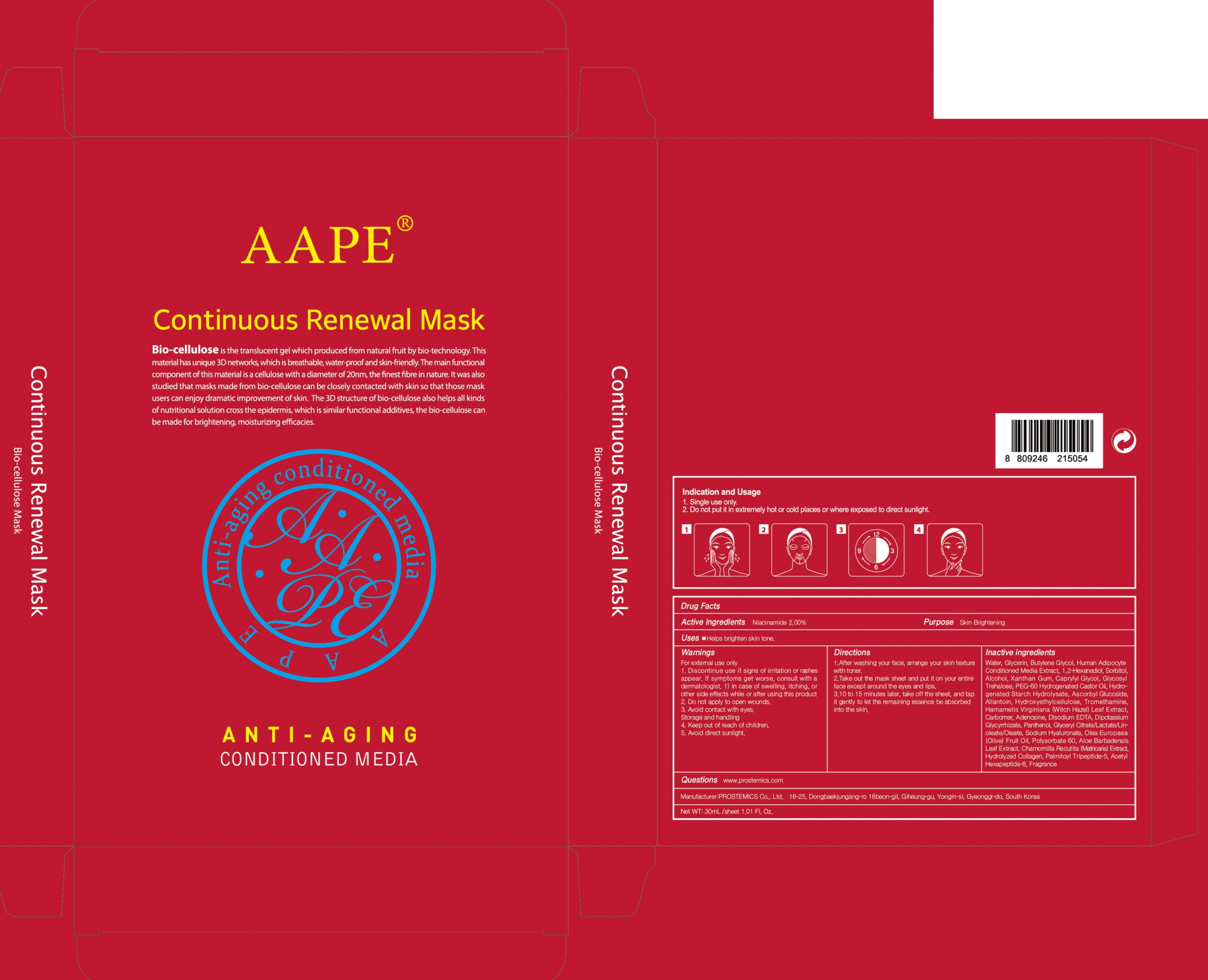 DRUG LABEL: AAPE Continuous Renewal Mask
NDC: 62041-240 | Form: PATCH
Manufacturer: PROSTEMICS Co., Ltd.
Category: otc | Type: HUMAN OTC DRUG LABEL
Date: 20190826

ACTIVE INGREDIENTS: Niacinamide 0.60 g/30 mL
INACTIVE INGREDIENTS: Water; Glycerin

ACTIVE INGREDIENT

Active ingredients: Niacinamide 2.00%

INACTIVE INGREDIENT

Inactive ingredients:
Water, Glycerin, Butylene Glycol, Human Adipocyte Conditioned Media Extract, 1,2-Hexanediol, Sorbitol, Alcohol, Xanthan Gum, Caprylyl Glycol, Glycosyl Trehalose, PEG-60 Hydrogenated Castor Oil, Hydrogenated Starch Hydrolysate, Ascorbyl Glucoside, Allantoin, Hydroxyethylcellulose, Tromethamine, Hamamelis Virginiana (Witch Hazel) Leaf Extract, Carbomer, Adenosine, Disodium EDTA, Dipotassium Glycyrrhizate, Panthenol, Glyceryl Citrate/Lactate/Linoleate/Oleate, Sodium Hyaluronate, Olea Europaea (Olive) Fruit Oil, Polysorbate 60, Aloe Barbadensis Leaf Extract, Chamomilla Recutita (Matricaria) Extract, Hydrolyzed Collagen, Palmitoyl Tripeptide-5, Acetyl Hexapeptide-8, Fragrance

PURPOSE

Purpose: Skin Brightening

WARNINGS

For external use only
1. Discontinue use if signs of irritation or rashes appear. If symptoms get worse, consult with a dermatologist. 1) In case of swelling, itching, or other side effects while or after using this product
2. Do not apply to open wounds.
3. Avoid contact with eyes.
Storage and handling
4. Keep out of reach of children.
5. Avoid direct sunlight.

KEEP OUT OF REACH OF CHILDREN

Uses

Helps brighten skin tone.

Directions

1. After washing your face, arrange your skin texture with toner.
2. Take out the mask sheet and put it on your entire face except around the eyes and lips.
3. Take off the sheet 10~15 min. later and tap it gently to let the remaining essence be absorbed into the skin.